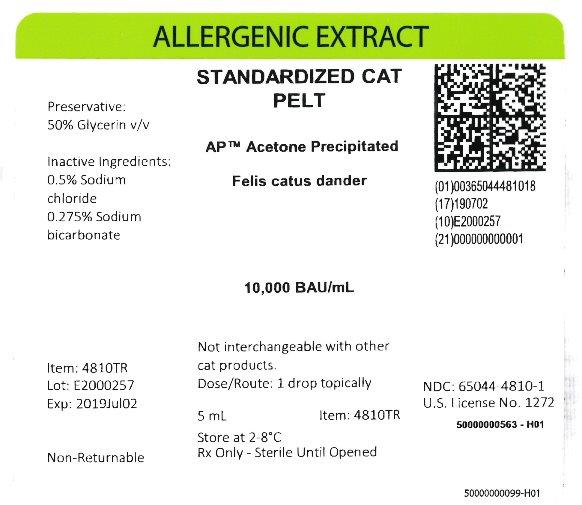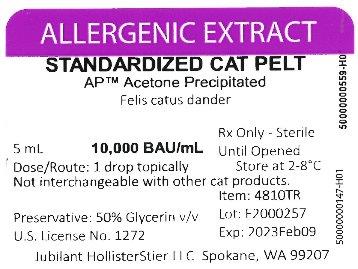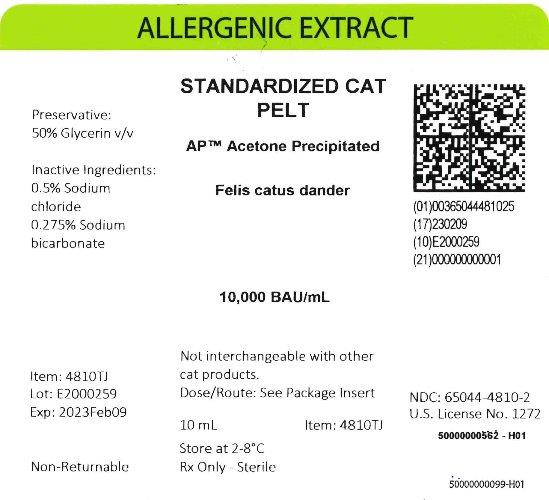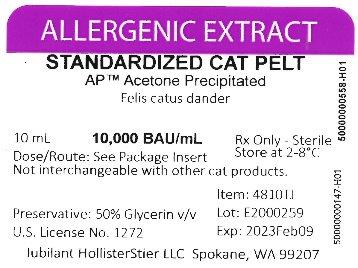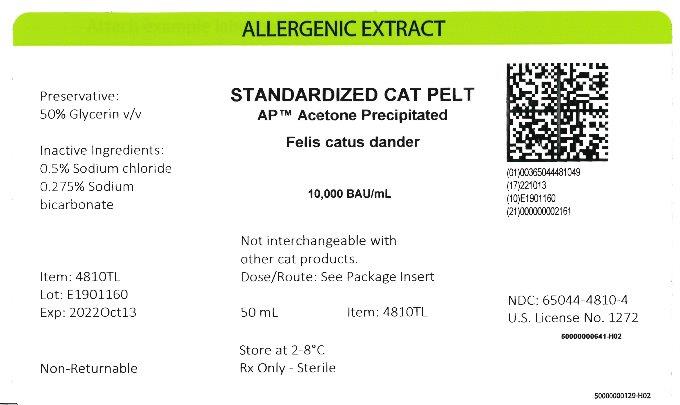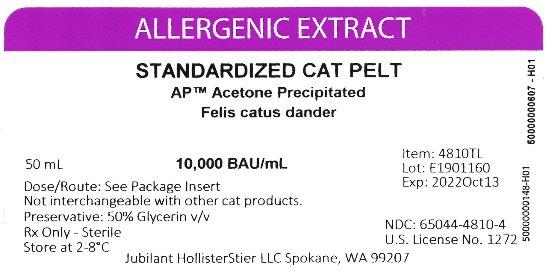 DRUG LABEL: Standardized Cat Pelt
NDC: 65044-4810 | Form: INJECTION, SOLUTION
Manufacturer: Jubilant HollisterStier LLC
Category: other | Type: STANDARDIZED ALLERGENIC
Date: 20251119

ACTIVE INGREDIENTS: FELIS CATUS DANDER 10000 [BAU]/1 mL
INACTIVE INGREDIENTS: GLYCERIN; SODIUM BICARBONATE; SODIUM CHLORIDE

ALLERGENIC EXTRACT STANDARDIZED CAT PELT AP ACETONE PRECIPITATED

WARNINGS

This product is intended for use only by licensed medical personnel experienced in administering allergenic extracts and trained to provide immediate emergency treatment in the event of a life-threatening reaction.
Allergenic extracts may potentially elicit a severe life-threatening systemic reaction, rarely resulting in death.1 Therefore, emergency measures and personnel trained in their use must be available immediately in the event of such a reaction. Patients should be instructed to recognize adverse reaction symptoms and cautioned to contact the physician's office if symptoms occur.
This standardized extract may be more potent than regular extracts and therefore is not directly interchangeable with our non-standardized extracts, or other manufacturers' products. Standardized pelt and hair extracts are manufactured from different source materials and are not interchangeable. Standardized cat extracts labeled in AU/mL are not interchangeable with extracts labeled in BAU/mL. See DESCRIPTION Section.
This product should never be injected intravenously.
Patients on non-selective beta blockers may be more reactive to allergens given for testing or treatment and may be unresponsive to the usual doses of epinephrine used to treat allergic reactions.5 Refer also the WARNINGS, PRECAUTIONS, ADVERSE REACTIONS and OVERDOSE Sections for further discussion.

DESCRIPTION

Allergenic extracts for subcutaneous injection and prick or puncture for diagnosis are sterile solutions containing the extractables of the source material and components of the extraction fluid. Standardized Cat Pelt is available as an extract from acetone precipitated source material in two different extraction fluids described below.

Source Material:
Cat Pelt source material consists of hair and whole epidermis which have undergone an acetone precipitation process. AP™ Acetone Precipitated Cat Pelt is derived from precipitate formed when acetone is added to an aqueous extract.

Extracting Fluids:
Glycero-Coca's: Contains 0.5% sodium chloride, 0.275% sodium bicarbonate, and 50% glycerin (v/v) as a preservative.

Product Concentration:
1. Bioequivalent Allergy Units. When originally licensed, standardized cat extracts containing 10 - 20 Fel d 1 units/mL were arbitrarily assigned 100,000 Allergy Units (AU)/mL. Subsequently, quantitative skin testing by the ID50EAL method 23 was used to determine that standardized cat extracts containing 10 to 19.9 Fel d 1 units/mL should be assigned 10,000 AU/mL rather than 100,000 AU/mL. To avoid possible confusion about this change in allergy unit assignment, the nomenclature changed for cat extracts, and such products are labeled in Bioequivalent Allergy Units (BAU/mL).
Each lot of Standardized Cat Pelt extract is standardized by quantitating the Fel d 1 content based on standards on file with the Center for Biologics Evaluation and Research (CBER) of the U.S.
Food and Drug Administration. Test extracts are diffused in agar containing standard anti-serum to Fel d 1 and compared to the diffusion of a reference cat allergen preparation.2 The potency of the extract is expressed as units of Fel d 1 per mL, and extracts containing 10-19.9 Fel d 1 units per mL are labeled at 10,000 BAU/mL.
It has been recognized that there are differences in the levels of non Fel d 1 allergens among standardized cat extracts which utilize different source materials. Isoelectric focusing (IEF) patterns have been shown to be predictive of the presence of non Fel d 1 allergens. Therefore, each lot of Standardized Cat Pelt is compared by IEF to a Cat Pelt Extract Reference and a Cat Hair Extract Reference on file with the CBER. The labeled name of the cat extract (i.e., Cat Hair Extract or Cat Pelt Extract) must be supported by matching the IEF profile of the corresponding reference.

2. Concentrate. Concentrate label terminology applies to allergenic extract mixtures where the individual allergens being combined vary in strength or the designation of strength.

e.g. | Concentrate
50% | Short Ragweed 1:20 w/v
25% | Std. Cat Pelt 10,000 BAU/mL
25% | Std. Mite D. farinae 10,000 AU/mL

Should the physician choose to calculate the actual strength of each component in the "Concentrate" mixture, the following formulation may be used:

Actual Allergen Strength in concentrate Mixture | = | Allergen Manufacturing Strength | x | % Allergen in Formulation (by volume or parts)

Ingredients:
Active ingredients are the allergen(s) noted on the vial label. Preservative is 50% (v/v) glycerin. Glycerinated extracts contain 0.5% sodium chloride, 0.275% sodium bicarbonate and 50% glycerin (v/v) as a preservative.

CLINICAL PHARMACOLOGY

13 The mechanisms by which hyposensitization is achieved are not completely understood. It has been shown that repeated injections of appropriate allergenic extracts will ameliorate the intensity of allergic symptoms upon contact with the allergen.6, 7, 8, 9 Clinical studies which address the efficacy of immunotherapy are available. The allergens which have been studied are cat, mite, and some pollen extracts.10, 11, 12, 13, 14, 15 IgE antibodies bound to receptors on mast cell membranes are required for the allergic reaction, and their level is probably related to serum IgE concentrations. Immunotherapy has been associated with decreased levels of IgE, and also with increases in allergen specific IgG "blocking" antibody. The histamine release response of circulating basophils to a specific allergen is reduced in some patients by immunotherapy, but the mechanism of this change is not yet clear. The relationships among changes in blocking antibody, reaginic antibody, and mediator-releasing cells, and successful immunotherapy need study and clarification.

INDICATIONS AND USAGE

3, 16, 17, 18 Allergenic extracts are indicated for use in diagnosis and immunotherapy of patients presenting symptoms of allergy (hay fever, rhinitis, etc.) to specific environmental allergens. The selection of allergenic extracts to be used should be based on a thorough and carefully taken history of hypersensitivity, and confirmed by skin testing.19, 20
The use of mixed or unrelated antigens for skin testing is not recommended since, in the case of a positive reaction, it does not indicate which component of the mix is responsible for the reaction, while, in the case of a negative reaction, it fails to indicate whether the individual antigens at full concentration would give a positive reaction. Utilization of such mixes for compounding a treatment may result, in the former case, in administering unnecessary antigens and, in the latter case, in the omission of a needed allergen.
Avoidance of allergens is to be advocated if possible, but cannot always be attained, e.g., allergy to cat dander in kennel owners and employees, cat breeders, research workers, veterinarians, etc.
Allergens to which a patient is extremely sensitive should not be included in treatment mixes with allergens to which there is much less sensitivity, but should be administered separately. This allows individualized and better control of dosage increases, including adjustments in dosage becoming necessary after severe reactions which may occur to the highly reactive allergen.

CONTRAINDICATIONS

There are no known absolute contraindications to immunotherapy. See PRECAUTIONS for pregnancy risks.
Patients with cardiovascular diseases or pulmonary diseases such as symptomatic asthma, and/or those who are receiving cardiovascular drugs such as beta blockers, may be at higher risk for severe adverse reactions. These patients may also be more refractory to the normal allergy treatment regimen. Patients should be treated only if the benefit of treatment outweighs the risks. 1
Any injections, including immunotherapy, should be avoided in patients with a bleeding tendency. Since there are differences of opinion concerning the possibility of routine immunizations exacerbating autoimmune diseases, immunotherapy should be given cautiously to patients with autoimmune diseases and only if the risk from exposure is greater than the risk of exacerbating the autoimmune process.

WARNINGS

See WARNINGS at the beginning of this instruction sheet. Allergenic extract should be temporarily withheld from patients or the dose adjusted downward if any of the following conditions exist: (1) severe symptoms of rhinitis and/or asthma; (2) infection or flu accompanied by fever; or (3) exposure to excessive amounts of clinically relevant allergen prior to a scheduled injection. Do not start immunotherapy during a period of symptoms due to exposure. Since the individual components of the extract are those to which the patient is allergic, and to which s/he will be exposed, typical allergic symptoms may follow shortly after the injection, particularly when the antigen load from exposure plus the injected antigen exceeds the patient's antigen tolerance.

THE CONCENTRATE SHOULD NOT BE INJECTED AT ANY TIME UNLESS TOLERANCE HAS BEEN ESTABLISHED. DILUTE CONCENTRATED EXTRACTS WITH STERILE DILUENT FOR INTRADERMAL TESTING. INJECTIONS SHOULD NEVER BE GIVEN INTRAVENOUSLY. Subcutaneous injection is recommended. Intracutaneous or intramuscular injection may produce large local reactions or be excessively painful. AFTER INSERTING NEEDLE SUBCUTANEOUSLY, BUT BEFORE INJECTING, ALWAYS WITHDRAW THE PLUNGER SLIGHTLY. IF BLOOD APPEARS IN THE SYRINGE, CHANGE NEEDLE AND GIVE THE INJECTION IN ANOTHER SITE

BOXED WARNING

IF CHANGING FROM HAIR TO PELT EXTRACTS OR VICE-VERSA: Hair and pelt extracts differ in their non Fel d 1 allergens and are not interchangeable. Therefore, if patients are switched from one type of cat extract to another, the initial dose should be based on skin tests as noted under DOSAGE AND ADMINISTRATION, 3. Immunotherapy.
IF THE PREVIOUS EXTRACT WAS NON-STANDARDIZED OR WAS STANDARDIZED AND LABELED IN ALLERGY UNITS PER mL (AU/mL): This standardized extract may be more potent than non-standardized extracts. Initiate therapy as though patient had not been receiving immunotherapy, or determine initial dose by skin test using serial dilutions of the extract. See PRECAUTIONS and DOSAGE AND ADMINISTRATION Sections.
IF CHANGING TO A DIFFERENT LOT OF EXTRACT: Even though it is the same formula and concentration, the first dose of the new extract should not exceed 50% of the last administered dose from the previous extract.
IF THE EXTRACT PREVIOUSLY USED WAS FROM ANOTHER MANUFACTURER: Since manufacturing processes and sources of raw materials differ among manufacturers, the interchangeability of extracts from different manufacturers cannot be insured. The starting dose of the extract therefore should be greatly decreased even though the extract is the same formula and dilution. Initiate therapy as though patient had not been receiving immunotherapy, or determine initial dose by skin test using serial dilutions of the extract. See DOSAGE AND ADMINISTRATION and ADVERSE REACTIONS Sections.
IF A PROLONGED PERIOD OF TIME HAS ELAPSED SINCE THE LAST INJECTION: Patients may lose tolerance for allergen injections during prolonged periods between doses. The duration of tolerance is an individual characteristic and varies from patient to patient. In general, the longer the lapse in the injection schedule, the greater dose reduction required. If the interval since last dose is over four weeks, perform skin tests to determine starting dose.
IF THE PREVIOUS EXTRACT WAS OUTDATED: The dating period for allergenic extracts indicates the time that they can be expected to remain potent under refrigerated storage conditions (2° - 8°C). During the storage of extracts, even under ideal conditions, some loss of potency occurs. For this reason, extracts should not be used beyond their expiration date. If a patient has been receiving injections of an outdated extract, he may experience excessive local or systemic reactions when changed to a new, and possibly more potent, extract. In general, the longer the material has been outdated, the greater the dose reduction necessary for the fresh extract.
IF CHANGING FROM ALUM-ADSORBED TO AQUEOUS OR GLYCERINATED EXTRACTS: When the patient previously has been receiving alum-adsorbed or alum-precipitated extract, the safest course is to start over as though the patient had not been receiving immunotherapy. See DOSAGE AND ADMINISTRATION and ADVERSE REACTIONS in product instructions.
IF ANY OTHER CHANGES HAVE BEEN MADE IN THE EXTRACT CONCENTRATE FORMULA: Changes other than those listed above may include situations such as a redistribution of component parts or percentages, a difference in extracting fluid (i.e., change from non-glycerin extracts to 50% glycerin extracts), combining two or more stock concentrates, or any other change. It should be recognized that any change in formula can affect a patient's tolerance of the treatment. The usual 1/2 of the previous dose for a new extract may produce an adverse reaction: extra dilutions are recommended whenever starting a revised formula. The greater the change, the greater the number of dilutions required.

WARNINGS

Proper selection of the dose and careful injection should prevent most systemic reactions. It must be remembered, however, that allergenic extracts are highly potent in sensitive individuals, and that systemic reactions of varying degrees of severity may occur, including urticaria, rhinitis, conjunctivitis, wheezing, coughing, angioedema, hypotension, bradycardia, pallor, laryngeal edema, fainting, or even anaphylactic shock and death. Patients should be informed of this, and the precautions should be discussed prior to immunotherapy. (See PRECAUTIONS below.) Severe systemic reactions should be treated as indicated in the ADVERSE REACTIONS Section. Refer to boxed WARNINGS Section.

PRECAUTIONS

1. GENERAL

Concentrated extracts must be diluted prior to use: See DOSAGE AND ADMINISTRATION Section below for detailed instructions on the dilution of allergenic extracts.
Any evidence of a local or generalized reaction requires a reduction in dosage during the initial stages of immunotherapy, as well as during maintenance therapy.
Allergenic extracts diluted with sterile Albumin Saline with Phenol (0.4%) diluent may be more potent than extracts diluted with diluents which do not contain stabilizers. When changing from non-stabilized or stabilized diluent, consider weaker initial dilutions for both intradermal testing and immunotherapy.
Sterile solutions, vials, syringes, etc. should be used and aseptic precautions observed in making dilutions.
To avoid cross-contamination, do not use the same needle to withdraw materials from vials of more than one extract, or extract followed by diluent.
A sterile tuberculin syringe graduated in 0.01 mL units should be used to measure each dose from the appropriate dilution. Aseptic techniques should always be employed when injections of allergenic extracts are being administered.
A separate sterile syringe should be used for each patient to prevent transmission of serum hepatitis and other infectious agents from one person to another.
Patient reactions to previous injections should be reviewed before each new injection. A conservative dosage schedule should be followed by the physician until a pattern of local responses is established which can be used to monitor increases in dosage.
Rarely, a patient is encountered who develops systemic reactions to minute doses of allergen and does not demonstrate increasing tolerance to injections after several months of treatment. If systemic reactions or excessive local responses occur persistently at very small doses, efforts at immunotherapy should be stopped.
PATIENTS SHOULD BE OBSERVED IN THE OFFICE FOR 30 MINUTES AFTER EACH TREATMENT INJECTION. Most severe reactions will occur within this time period, and rapid treatment measures should be instituted. See ADVERSE REACTIONS Section for such treatment measures.

2. INFORMATION FOR PATIENTS

Patients should be instructed in the recognition of adverse reactions to immunotherapy, and in particular, to the symptoms of shock. Patients should be made to understand the importance of a 30 minute observation period, and be warned to return to the office promptly if symptoms occur after leaving.

3. DRUG INTERACTIONS

Patients on non-selective beta blockers may be more reactive to allergens given for testing or treatment and may be unresponsive to the usual doses of epinephrine used to treat allergic reactions.5
Certain medications may lessen the skin test wheal and erythema responses elicited by allergens and histamine for varying time periods. Conventional antihistamines should be discontinued at least 5 days before skin testing. Long acting antihistamines should be discontinued for at least 3 weeks prior to skin testing.24 Topical steroids should be discontinued at the skin test site for at least 2-3 weeks before skin testing. 24, 25 Tricyclic antidepressants such as Doxepin should be withheld for at least 7 days before skin testing.26 Topical local anesthetics may suppress the flare responses and should be avoided in skin test sites.27

4. CARCINOGENESIS, MUTAGENESIS, IMPAIRMENT OF FERTILITY

Long-term studies in animals have not been conducted with allergenic extracts to determine their potential for carcinogenicity, mutagenicity or impairment of fertility.

5. PREGNANCY

Animal reproduction studies have not been conducted with allergenic extracts. It is also not known whether allergenic extracts can cause fetal harm when administered to a pregnant woman or can affect reproduction capacity. Allergenic extracts should be given to a pregnant woman only if clearly needed.
For women who have been getting maintenance doses of allergen without side effect, the occurrence of pregnancy is not an indication to stop immunotherapy.

6. NURSING MOTHERS

There are no current studies on secretion of the allergenic extract components in human milk or effect on the nursing infant. Because many drugs are excreted in human milk, caution should be exercised when allergenic extracts are administered to a nursing woman.

7. PEDIATRIC USE

Since dosage for the pediatric population is the same as for adults 3, 4 the larger volumes of solution may produce excessive discomfort. Therefore, in order to achieve the total dose required, the volume of the dose may need to be divided into more than one injection per visit.

8. GERIATRIC USE

The reactions from immunotherapy can be expected to be the same in elderly patients as in younger ones. Elderly patients may be more likely to be on medication that could block the effect of epinephrine which could be used to treat serious reactions, or they could be more sensitive to the cardiovascular side effect of epinephrine because of pre-existing cardiovascular disease.28

ADVERSE REACTIONS

1. Local Reactions
Some erythema, swelling or pruritus at the site of injection are common, the extent varying with the patient. Such reactions should not be considered significant unless they persist for at least 24 hours. Local reactions (erythema or swelling) which exceed 4-5 cm in diameter are not only uncomfortable, but also indicate the possibility of a systemic reaction if dosage is increased. In such cases the dosage should be reduced to the last level not causing the reaction and maintained at this level for two or three treatments before cautiously increasing again. Large persistent local reactions may be treated by local cold, wet dressings and/or the use of oral antihistamines. They should be considered a warning of possible severe systemic reactions and an indication of the need for temporarily reduced dosages. A mild burning immediately after the injection is to be expected. This usually leaves in 10 to 20 seconds.

2. Systemic Reactions
With careful attention to dosage and administration, systemic reactions occur infrequently, but it cannot be overemphasized that in sensitive individuals, any injection could result in anaphylactic shock. Therefore, it is imperative that physicians administering allergenic extracts understand and be prepared for the treatment of severe reactions. Other possible systemic reactions which may occur in varying degrees of severity are laryngeal edema, fainting, pallor, bradycardia, hypotension, angioedema, cough, wheezing, conjunctivitis, rhinitis, and urticaria. Adverse reaction frequency data for allergenic extract administration for testing and treatment show that risk is low. 1, 21
If a systemic or anaphylactic reaction does occur, apply a tourniquet above the site of injection and inject 1:1000 epinephrine-hydrochloride intramuscularly or subcutaneously into the opposite arm. Loosen the tourniquet at least every 10 minutes. Do not obstruct arterial blood flow with the tourniquet.

EPINEPHRINE DOSAGE
ADULT: 0.3 to 0.5 mL should be injected. Repeat in 5 to 10 minutes if necessary.
PEDIATRIC: The usual initial dose is 0.01 mg (mL) per kg body weight or 0.3 mg (mL) per square meter of body surface area. Suggested dosage for infants to 2 years of age is 0.05 mL to 0.1 mL; for children 2 to 6 years, 0.15 mL; and children 6 to 12 years, 0.2 mL. Single pediatric doses should not exceed 0.3 mg (mL). Doses may be repeated as frequently as every 20 minutes, depending on the severity of the condition and the response of the patient.
After administration of epinephrine, profound shock or vasomotor collapse should be treated with intravenous fluids, and possibly vasoactive drugs. Airway patency should be insured. Oxygen should be given by mask. Intravenous antihistamine, theophylline and/or corticosteroids may be used if necessary after adequate epinephrine and circulatory support has been given.
Emergency resuscitation measures and personnel trained in their use should be available immediately in the event of a serious systemic or anaphylactic reaction not responsive to the above measures [Ref. J. Allergy and Clinical Immunology, 77(2):p. 271-273, 1986].
Rarely are all of the above measures necessary; the tourniquet and epinephrine usually produce prompt responses. However, the physician should be prepared in advance for all contingencies. Promptness in beginning emergency treatment measures is of utmost importance.
Severe systemic reactions mandate a decrease of at least 50% in the next dose, followed by cautious increases. Repeated systemic reactions, even of a mild nature, are sufficient reason for the cessation of further attempts to increase the reaction-causing dose.

3. Adverse Event Reporting
Report all adverse events to Jubilant HollisterStier LLC Customer Technical Services Department at 1 (800) 992-1120. A voluntary adverse event reporting system for health professionals is available through the FDA MEDWATCH program. Preprinted forms (FDA Form 3500) are available from the FDA by calling 1 (800) FDA-1088. Completed forms should be mailed to MEDWATCH, 5600 Fisher Lane, Rockville, MD 20852-9787 or Fax to: 1 (800) FDA-0178.

OVERDOSAGE

See ADVERSE REACTIONS Section.

DOSAGE AND ADMINISTRATION

3, 16, 17 ,18

1. General

Sterile aqueous diluent containing human serum albumin is recommended when preparing dilutions of the concentrate for intradermal testing or immunotherapy. Dilutions should be made accurately and aseptically, using sterile diluent, vials, syringes, etc. Mix thoroughly and gently by rocking or swirling. Parenteral drug products should be inspected visually for particulate matter and discoloration prior to administration whenever solution and container permit.

2. Diagnosis

To identify highly sensitive individuals and as a safety precaution, it is recommended that a prick or puncture test using a drop of the extract concentrate be performed prior to initiating intradermal testing. Prick tests are performed by placing a drop of extract on the skin and piercing through the drop into the skin with a slight lifting motion. Puncture tests are performed by placing a drop of extract on the skin and piercing through the drop perpendicular to the skin with a device such as a Prick Lancetter. After about 1 minute the extract may be wiped away with a dry sponge. The diameter of wheal and erythema reactions are measured 15 minutes after the prick or puncture is made, and the sensitivity class of the patient determined by the table presented at the end of the diagnosis section. Less sensitive individuals (Class 0 to 1+) can be tested intradermally with the recommended dilutions of the extract concentrate (see Intradermal Testing). The skin test concentration of 10,000 BAU/mL (10-19.9 Fel d 1 Units/mL) in dropper vials is used for prick or puncture testing. Puncture tests performed on 15 highly sensitive subjects showed the following:

Product | Mean Sum of Wheal ± 1 Std. Dev (mm) | Mean Sum of Erythema ± Std. Dev. (mm)
Standardized Cat Pelt | 13.9 ± 4.3 | 67.3 ± 13.3

The sum of a skin response is the sum of the longest diameter and the midpoint orthogonal diameter.

Intradermal endpoint titration (IET) tests were completed using the same 15 subjects to determine the mean concentration required to produce a ∑E of 50mm (D50). That concentration contained 0.042 BAU/mL (range 0.002 to 0.890 BAU/mL).

Intradermal extract should be used as follows:

Intradermal Tests should be done only on patients with a negative prick or puncture test. Patients who do not react to a valid prick or puncture test should be tested intradermally with 0.02 to 0.05 mL of a 100 BAU/mL extract solution. If this test is negative, a second intradermal test may be performed using a 1,000 BAU/mL extract solution. If the intradermal dilutions were prepared from glycerinated concentrate, the negative control used with this latter dilution should contain 5% glycerol. Skin tests are graded in terms of the wheal and erythema response noted at 15 minutes. Wheal and erythema size may be recorded by actual measurement of the extent of both responses. Refer to the following table to determine the skin test sensitivity class. The corresponding ∑E (sum of the longest diameter and the mid-point orthogonal diameters of erythema) is also presented.

Class | Wheal Diameter | Erythema Diameter | Corresponding ∑E
0 | <5 mm | <5 mm | <10 mm
± | 5-10 mm | 5-10 mm | 10-20 mm
1+ | 5-10 mm | 11-20 mm | 20-40 mm
2+ | 5-10 mm | 21-30 mm | 40-60 mm
3+ | 10-15 mma | 31-40 mm | 60-80 mm
4+ | >15 mmb | >40 mm | >80 mm

a. or with pseudopods
b. or with many pseudopods

3. Immunotherapy

Allergen extracts should be administered using a sterile syringe with 0.01 mL gradations and a 25-27 gauge x 1/2" to 5/8" needle. The injections are given subcutaneously. The most common sites of injection are the lateral aspect of the upper arm or thigh. Intracutaneous or intramuscular injections may produce large local reactions which may be very painful.

Dosage of allergenic extracts is a highly individualized matter and varies according to the degree of sensitivity of the patient, his clinical response, and tolerance to the extract administered during the early phases of an injection regimen. The starting dose should be based on skin tests of the extract to be used for immunotherapy. To prepare dilutions for intradermal and therapeutic use, make a 1:10 dilution by adding 1.0 mL of the concentrate to 9.0 mL of sterile aqueous diluent. Subsequent serial dilutions are made in a similar manner. (See Table I.) To determine the starting dose, begin intradermal testing with the most dilute extract preparation. Inject 0.02 mL and read the reaction after 15 minutes. Intradermal testing is continued with increasing concentrations of the extract until a reaction of 10-20 mm erythema (∑E 20-40 mm) and/or a 5 mm wheal occurs. This concentration at a dose of 0.03 mL then can serve as a starting dose for immunotherapy and be increased by 0.03 mL to as high as 0.12 mL increments each time until 0.3 mL is reached, at which time a dilution 10 times as strong can be used, starting with 0.03 mL. Proceed in this way until a tolerance dose is reached or symptoms are controlled. Suggested maintenance dose is 0.2 mL of the concentrate. Occasionally, higher doses are necessary to relieve symptoms. Special caution is required in administering doses greater than 0.2 mL. The interval between doses normally is 3 to 7 days.

This is offered as a suggested schedule for average patients and will be satisfactory in most cases. However, the degree of sensitivity varies in many patients. The size of the dose should be adjusted and should be regulated by the patient's tolerance and reaction. The size of the dose should be decreased if the previous injection resulted in marked local or the slightest general reaction. Another dose should never be given until all local reactions resulting from the previous dose have disappeared.

In some patients, the dosage may be increased more rapidly than called for in the schedule. In seasonal allergies, treatment should be started and the interval between doses regulated so that at least the first 20 doses will have been administered by the time symptoms are expected. Thus, the shorter the interval between the start of immunotherapy and the expected onset of symptoms, the shorter the interval between each dose. Some patients may even tolerate daily doses. A maintenance dose, the largest dose tolerated by the patient that relieves symptoms without producing undesirable local or general reactions is recommended for most patients. The upper limits of dosage have not been established; however, doses larger than 0.2 mL of the glycerinated concentrate may be painful due to the glycerin content. The dosage of allergenic extract does not vary significantly with the respiratory allergic disease under treatment. The size of this dose and the interval between doses will vary and can be adjusted as necessary. Should symptoms develop before the next injection is scheduled, the interval between doses should be decreased. Should allergic symptoms or local reactions develop shortly after the dose is administered, the size of the dose should be decreased. In seasonal allergies, it is often advisable to decrease the dose to one-half or one-quarter of the maximum dose previously attained if the patient has any seasonal symptoms. The interval between maintenance doses can be increased gradually from one week to 10 days, to two weeks, to three weeks, or even to four weeks if tolerated. Repeat the doses at a given interval three or four times to check for untoward reactions before further increasing the interval. Protection is lost rapidly if the interval between doses is more than four weeks. (See WARNINGS Section.) The usual duration of treatment has not been established. A period of two or three years of injection therapy constitutes an average minimum course of treatment.

TABLE 1
TEN-FOLD DILUTION SERIES
Standardized Extracts Labeled 10,000 BAU/mL

Dilution | Extract | + Diluent | = | BAU/mL Concentration
0 | Concentrate | +0 mL |  | 10,000
1 | 1 mL concentrate | +9 mL | = | 1,000
2 | 1 mL dilution #1 | +9 mL | = | 100
3 | 1 mL dilution #2 | +9 mL | = | 10
4 | 1 mL dilution #3 | +9 mL | = | 1
5 | 1 mL dilution #4 | +9 mL | = | 0.1
6 | 1 mL dilution #5 | +9 mL | = | 0.01
7 | 1 mL dilution #6 | +9 mL | = | 0.001

(4) PEDIATRIC USE

The dose for the pediatric population is the same as for adults. (See PRECAUTIONS.)

(5) GERIATRIC USE

The dose for elderly patients is the same as for adults patients under 65. 28

HOW SUPPLIED

Standardized Cat Pelt allergenic extract is supplied for diagnostic and therapeutic use:
Diagnostics:
Prick or puncture testing, 10,000 BAU/mL [50% glycerin (v/v)] in 5 mL dropper vial.
Bulk Therapeutics; multiple dose vials in 50% glycerin (v/v).
10 mL vial, 10,000 BAU/mL
30 mL vial, 10,000 BAU/mL
50 mL vial, 10,000 BAU/mL

STORAGE

The expiration date of the Standardized Cat Pelt extract containing 10,000 BAU/mL is listed on the container label. The extract should be stored at 2° - 8°C. Dilutions of the BAU/mL concentrates are less stable and, if loss of potency is suspected, should be checked by skin testing with equal bioequivalent allergy units of a freshly prepared dilution on known cat allergic individuals.

LIMITED WARRANTY

A number of factors beyond our control could reduce the efficacy of this product or even result in an ill effect following its use. These include storage and handling of the product after it leaves our hands, diagnosis, dosage, method of administration and biological differences in individual patients. Because of these factors, it is important that this product be stored properly and that the directions be followed carefully during use. No warranty, express or implied, including any warranty of merchantability or fitness, is made. Representatives of the Company are not authorized to vary the terms or the contents of any printed labeling, including the package insert, for this product except by printed notice from the Company's headquarters. The prescriber and user of this product must accept the terms hereof.

REFERENCES

1. Lockey, Richard F., Linda M. Benedict, Paul C. Turkeltaub, Samuel C. Bukantz. Fatalities from immunotherapy (IT) and skin testing (ST). J. Allergy Clin. Immunol. 79 (4): 660-677, April 1987.
2. Assay for Cat Allergen I. Manual of Methods, Laboratory of Allergenic Products. Center for Biologics Evaluation and Research. Oct. 1993.
3. Patterson, Roy, et al. Allergy Principles and Practice, 2nd ed. E. Middleton, Jr., C.E. Reed, E.F. Ellis, Ed. C.V. Mosby Co. St. Louis, MO, 1983. Chapter 52.
4. Levy, D.A., L.M. Lichtenstein, E.O. Goldstein, K. Ishizaka. Immunologic and cellular changes accompanying the therapy of pollen allergy. J. Clinical Investigation. 50:360, 1971.
5. Jacobs, R.L., G.W. Rake, Jr., et al. Potentiated anaphylaxis in patients with drug-induced beta-adrenergic blockade. J. Allergy and Clin. Immunol. 68 (2): 125-127, August 1981.
6. Lowell, F.C., W. Franklin. A "double-blind" study of treatment with aqueous allergenic extracts in cases of allergic rhinitis. J. Allergy. 34 (2): 165-182, 1983.
7. Lowell, F.C., W. Franklin. A double-blind study of the effectiveness and specificity of injection therapy in ragweed hay fever. N. Eng. J. Med. 273 (13): 675-679, 1965.
8. Zavazal, V., A. Stajner. Immunologic changes during specific treatment of the atopic state. II. Acta. Allergol. 25 (1): 11-17, 1970.
9. Reisman, R.E., J.I. Wypych, E.E. Arbesman. Relationships of immunotherapy, seasonal pollen exposure and clinical response to serum concentrations of total IgE and ragweed-specific IgE. Int. Arch. Allergy Appl. Immunol. 48 (6): 721-730, 1975.
10. Ohman, J.L., S.R. Findlay, K. Leiterman. Immunotherapy in cat-induced asthma: double-blind trial with evaluation of in vivo and vitro responses. J. Allergy Clin. Immunol. 74:230, 1984.
11. Sundin, B., G. Lilja, V. Graff-Lonnevig, G. Hedlin, H. Heilborn, K. Norrlind, K-O Pegelow, H. Lowenstein. Immunotherapy with partially purified and standardized animal dander extracts. I Clinical results from a double-blind study on patients with animal dander asthma. J. Allergy Clin. Immunol. 77:478, 1986.
12. Chapman, M.D., T.A.E. Platts-Mills, M. Gabriel, H.K. Ng, W.G.L. Allen, L.E. Hill, A.J. Nunn. Antibody response following prolonged hyposensitization with Dermatophagoides pteronyssinus extract. Int. Arch. Allergy Appl. Immunol. 61: 431-440, 1980.
13. Norman, P.S. Postgraduate Course Presentation. An overview of immunotherapy, implications for the future. J. Allergy Clin. Immunol. 65 (2): 87-96, 1980.
14. Norman, P.S., W.L. Winkenwerder. Maintenance immunotherapy in ragweed hay fever. J. Allergy. 74: 273-282, 1971.
15. Norman, P.S., W.L. Winkenwerder, L.M. Lichtenstein. Immunotherapy of hay fever with ragweed Antigen E; comparisons with whole pollen extract and placebos. J. Allergy. 42: 93-108, 1968.
16. Sheldon, J.M., R.G. Lovell, K.P. Matthews. A Manual of Clinical Allergy. Second Edition. W.B. Saunders. Philadelphia, pp. 107-112, 1967.
17. Sherman, W.B. Hypersensitivity Mechanism and Management. W.B. Sanders. Philadelphia, pp. 169-172, 1968.
18. Swineford, O. Asthma and Hay Fever. Charles C. Thomas. Springfield, IL, pp. 148-155, 1971.
19. Pauli, G., J.C. Bessot, R. Thierry, A. Lamensons. Correlation between skin tests, inhalation tests and specific IgE in a study of 120 subjects to house dust and D. pteronyssinus. Clin. Allergy. :337, 1977.
20. Murray, A.B., A.C. Ferguson B.J. Morrison. Diagnosis of house dust mite allergy in asthmatic children: What constitutes positive history? J. Allergy Clin. Immunol. 71:21, 1983.
21. Turkeltaub, Paul C., Peter J. Gergen. The risk of adverse reactions from percutaneous prick-puncture allergen skin testing, venipuncture, and body measurements: Data from the second National Health and Nutrition Examination Survey 1976-80 (NHANES II).
J. Allergy Clin. Immunol. 84 (6): 886-890, Dec. 1989.
22. DuBuske, L.M., C.J. Ling, A.L. Sheffer. Special problems regarding allergen immunotherapy. Immunol. Allergy Clin. North Am. (USA). 12(1): 145-175, 1992.
23. Turkeltaub, Paul C., Suresh Rastogi, Harold Baer. Skin test method for evaluation of subject sensitivity to standardized allergenic extracts and for assignment of Allergy Units to reference preparations using the ID50EAL Method. Manual of Methods, Center for Biologics Evaluation and Research. May 1986.
24. Pipkorn, Ulf. Pharmacological influence of anti-allergic medication on In Vivo allergen testing. Allergy. 43: 81-86, 1988.
25. Andersson, M. U. Pipkorn. Inhibition of the dermal immediate allergic reaction through prolonged treatment with topical glucocorticosteroids. Journal Allergy Clinical Immunology. 79 (2): 345-349. February 1987.
26. Rao, Kamineni S., et al. Duration of suppressive effect of tricyclic anti-depressants on histamine induced wheal and flare reactions on human skin. Journal Allergy Clinical Immunology. 82: 752-757, November 1988.
27. Pipkorn, Ulf, M. Andersson. Topical dermal anesthesia inhibits the flare but not the wheal response to allergen and histamine in the skin prick test. Clinical Allergy. 17: 307-311, 1987.
28. Peebles, Ray Stokes, Jr., B. Bochner, Howard J. Zeitz, ed. Anaphylaxis in the elderly. Immunology and Allergy Clinics of North America. 13 (3): 627-646, August 1993.